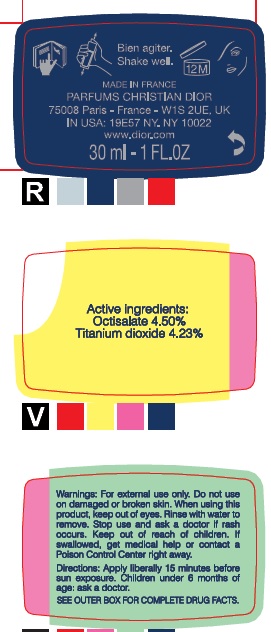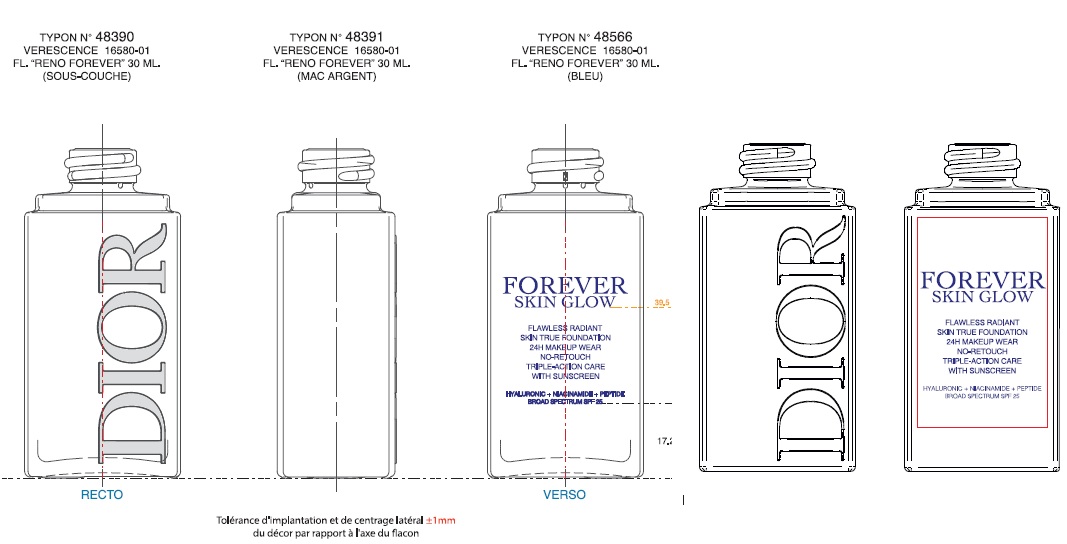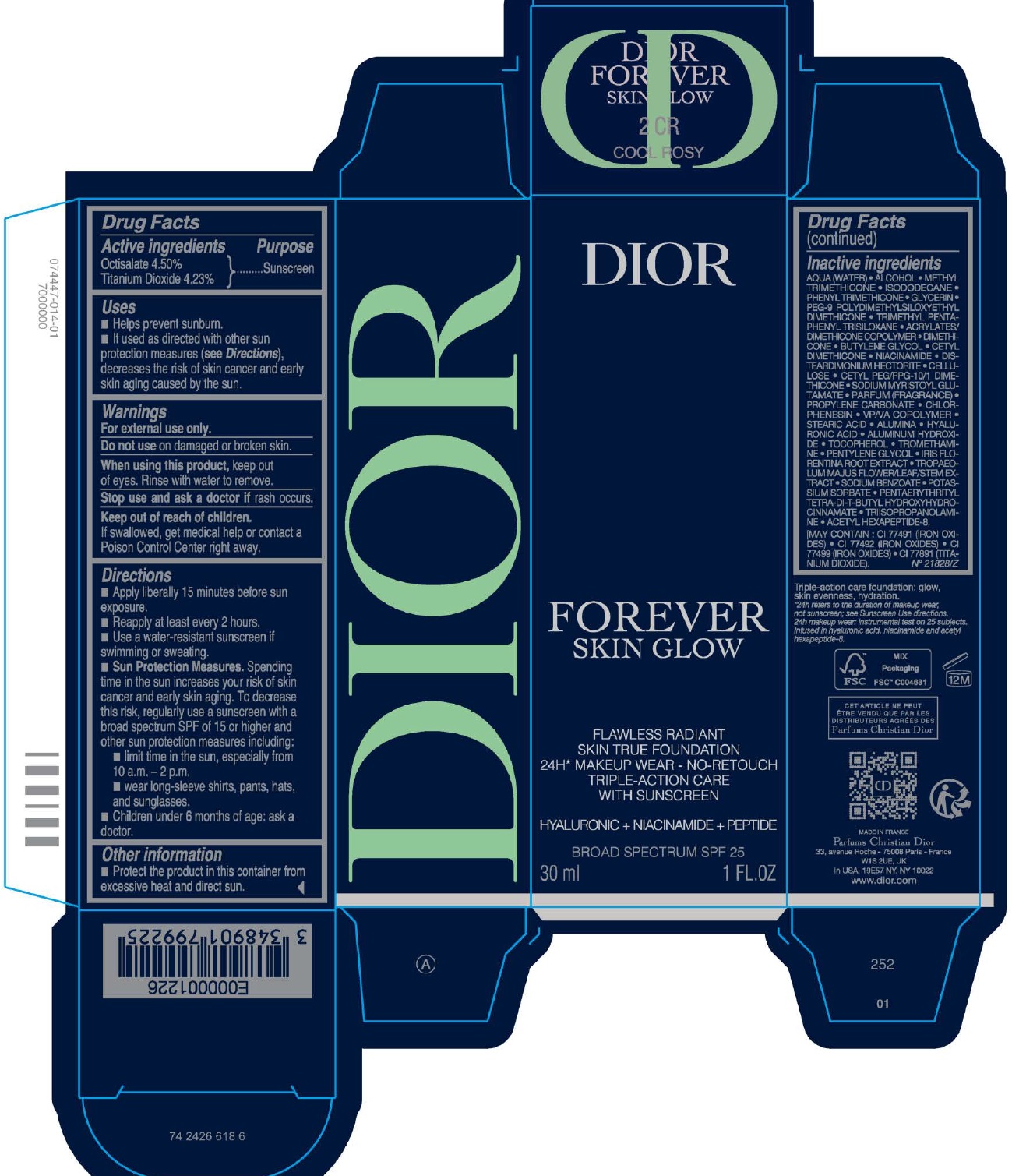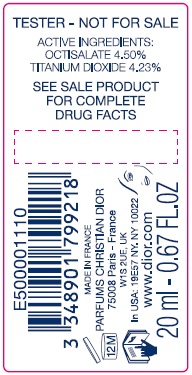 DRUG LABEL: Dior Forever Skin Glow Flawless Radiant Skin True Foundation SPF 25 2CR Cool Fosy
NDC: 61957-3312 | Form: EMULSION
Manufacturer: Parfums Christian Dior
Category: otc | Type: HUMAN OTC DRUG LABEL
Date: 20260119

ACTIVE INGREDIENTS: OCTISALATE 45 mg/1 mL; TITANIUM DIOXIDE 42.3 mg/1 mL
INACTIVE INGREDIENTS: COPOVIDONE K25-31; STEARIC ACID; ALUMINUM OXIDE; HYALURONIC ACID; ALUMINUM HYDROXIDE; TOCOPHEROL; TROMETHAMINE; PENTYLENE GLYCOL; IRIS X GERMANICA NOTHOVAR. FLORENTINA ROOT; TROPAEOLUM MAJUS FLOWERING TOP; SODIUM BENZOATE; POTASSIUM SORBATE; TRIISOPROPANOLAMINE; ACETYL HEXAPEPTIDE-8 AMIDE; WATER; ALCOHOL; METHYL TRIMETHICONE; ISODODECANE; PHENYL TRIMETHICONE; GLYCERIN; PEG-9 POLYDIMETHYLSILOXYETHYL DIMETHICONE; TRIMETHYL PENTAPHENYL TRISILOXANE; DIMETHICONE; BUTYLENE GLYCOL; NIACINAMIDE; DISTEARDIMONIUM HECTORITE; POWDERED CELLULOSE; SODIUM MYRISTOYL GLUTAMATE; PROPYLENE CARBONATE; CHLORPHENESIN

Dior Forever Skin Glow Flawless Radiant Skin True Foundation SPF 25 2CR Cool Fosy

Active ingredients

Octisalate 4.50%

Titanium Dioxide 4.23%

Purpose

Sunscreen

Uses

- Helps prevent sunburn.
- If used as directed with other sun protection measures (see Directions), decreases the risk of skin cancer and early skin aging caused by the sun.

Warnings

For external use only.

Do not use

on damaged or broken skin.

When using this product,

keep out of eyes. Rinse with water to remove.

Stop use and ask a doctor if

rash occurs.

Keep out of reach of children.

If swallowed, get medical help or contact a Poison Control Center right away.

Directions

- Apply liberally 15 minutes before sun exposure.
- Reapply at least every 2 hours.
- Use a water-resistant sunscreen if swimming or sweating.
- Sun Protection Measures.Spending time in the sun increases your risk of skin cancer and early skin aging. To decrease this risk, regularly use a sunscreen with a broad spectrum SPF of 15 or higher and other sun protection measures including:
- limit time in the sun, especially from 10 a.m. - 2 p.m.
- wear long-sleeve shirts, pants, hats, and sunglasses.
- Children under 6 months of age: ask a doctor.

Other information

- Protect the product in this container from excessive heat and direct sun.

Inactive ingredients

AQUA (WATER) • ALCOHOL • METHYL TRIMETHICONE • ISODODECANE • PHENYL TRIMETHICONE • GLYCERIN • PEG-9 POLYDIMETHYLSILOXYETHYL DIMETHICONE • TRIMETHYL PENTAPHENYL TRISILOXANE • ACRYLATES/DIMETHICONE COPOLYMER • DIMETHICONE • BUTYLENE GLYCOL • CETYL DIMETHICONE • NIACINAMIDE • DISTEARDIMONIUM HECTORITE • CELLULOSE • CETYL PEG/PPG-10/1 DIMETHICONE • SODIUM MYRISTOYL GLUTAMATE • PARFUM (FRAGRANCE) • PROPYLENE CARBONATE • CHLORPHENESIN • VP/VA COPOLYMER • STEARIC ACID • ALUMINA • HYALURONIC ACID • ALUMINUM HYDROXIDE • TOCOPHEROL • TROMETHAMINE • PENTYLENE GLYCOL • IRIS FLORENTINA ROOT EXTRACT • TROPAEOLUM MAJUS FLOWER/LEAF/STEM EXTRACT • SODIUM BENZOATE • POTASSIUM SORBATE • PENTAERYTHRITYL TETRA DI-BUTYL HYDROXYHYDROCINNAMATE • TRIISOPROPANOLAMINE • ACETYL HEXAPEPTIDE-8.
[MAY CONTAIN : CI 77491 (IRON OXIDES), CI 77492 (IRON OXIDES) , CI 77499 (IRON OXIDES), CI 77891 (TITANIUM DIOXIDE)]. N° 21828/Z